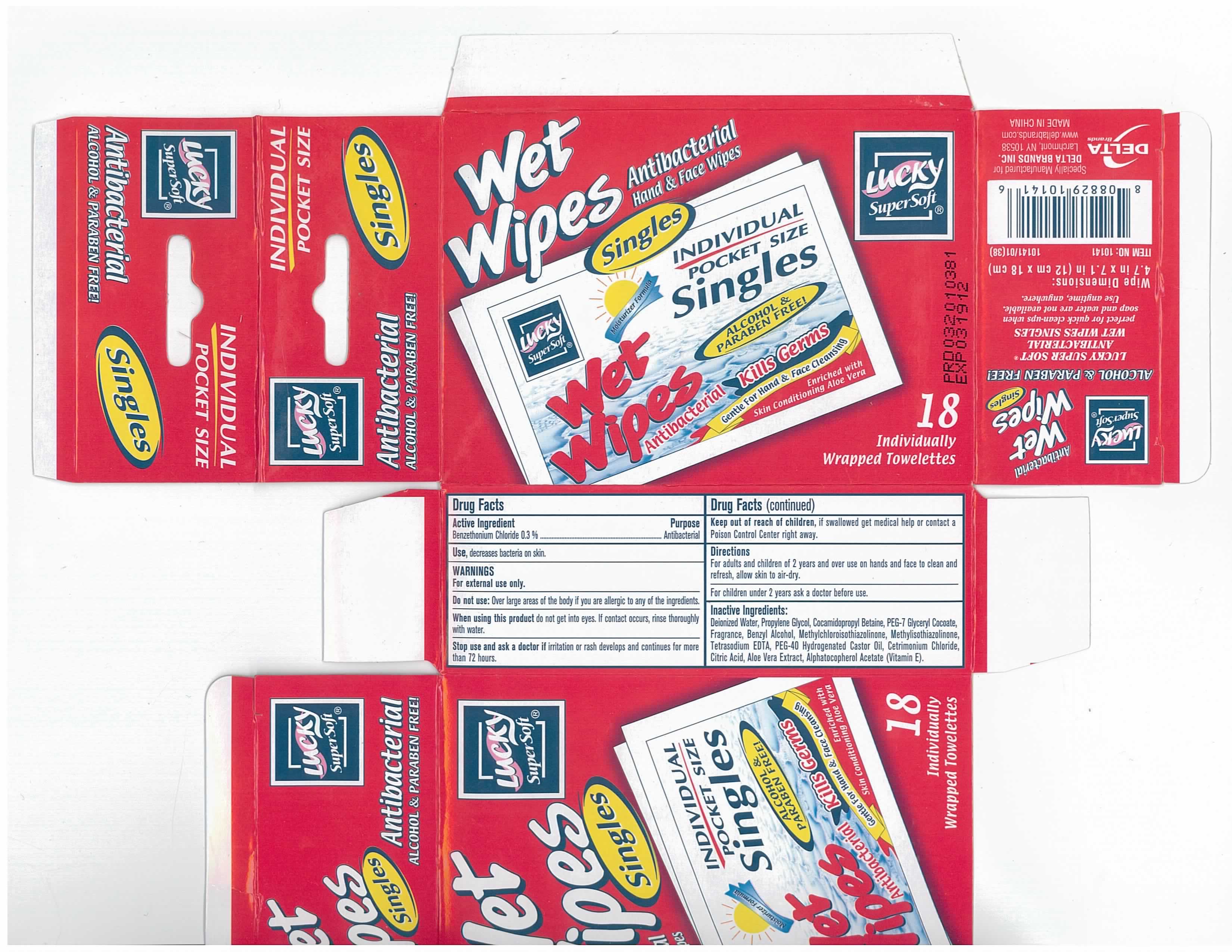 DRUG LABEL: Wet Wipes
NDC: 20276-433 | Form: SWAB
Manufacturer: Delta Brands, Inc
Category: otc | Type: HUMAN OTC DRUG LABEL
Date: 20110516

ACTIVE INGREDIENTS: BENZETHONIUM CHLORIDE 0.3 mL/1 1
INACTIVE INGREDIENTS: WATER; PROPYLENE GLYCOL; COCAMIDOPROPYL BETAINE; BENZYL ALCOHOL; METHYLCHLOROISOTHIAZOLINONE; METHYLISOTHIAZOLINONE; EDETATE SODIUM; CETRIMONIUM CHLORIDE; CITRIC ACID MONOHYDRATE; ALOE VERA LEAF; ALPHA-TOCOPHEROL ACETATE

Drug Facts

Active Ingredient

Benzethonium Chloride 0.3%

Purpose

Antibacterial

Uses

decreases bacteria on the skin

Warnings

For external use only

Do not use

Over large areas of the body if you are allergic to any of the ingredients

When using this product do not get into eyes.
If contact occurs, rinse thoroughly with water.

Stop use

Stop use and ask a doctor if irritation or rash develops and continues for more than 72 hours

Keep out of reach of children, if swallowed get medical help or contact a Poison Control Center right away.

Directions

For adults and children 2 years and over use on hands and face to clean and refresh, allow skin to air dry. For children under 2 years of age ask a doctor before use.

Inactive Ingredients

Water, Propylene Glycol, Cocamidopropyl Betaine, PEG-7 Glyceryl Cocoate, Fragrance, Benzyl Alcohol, Methylchloroisothiazolinine, Methylisothiazolinone, Tetrasodium EDTA, PEG-40 Hydrogenated Castor Oil, Cetrimonium Chloride, Citric Acid, Aloe Vera Extract, Alphatocopherol Acetate (Vitamin E)

Package Label